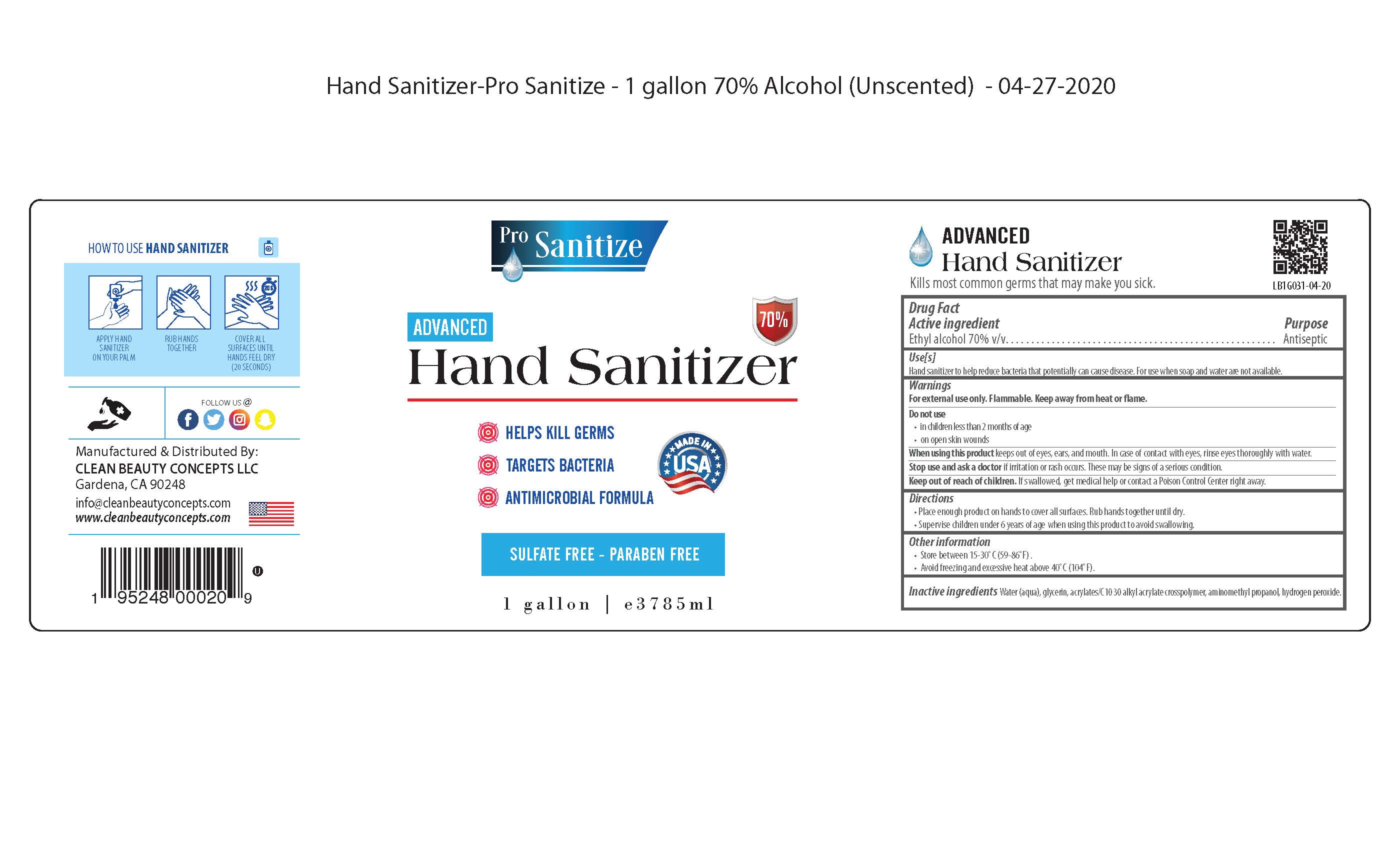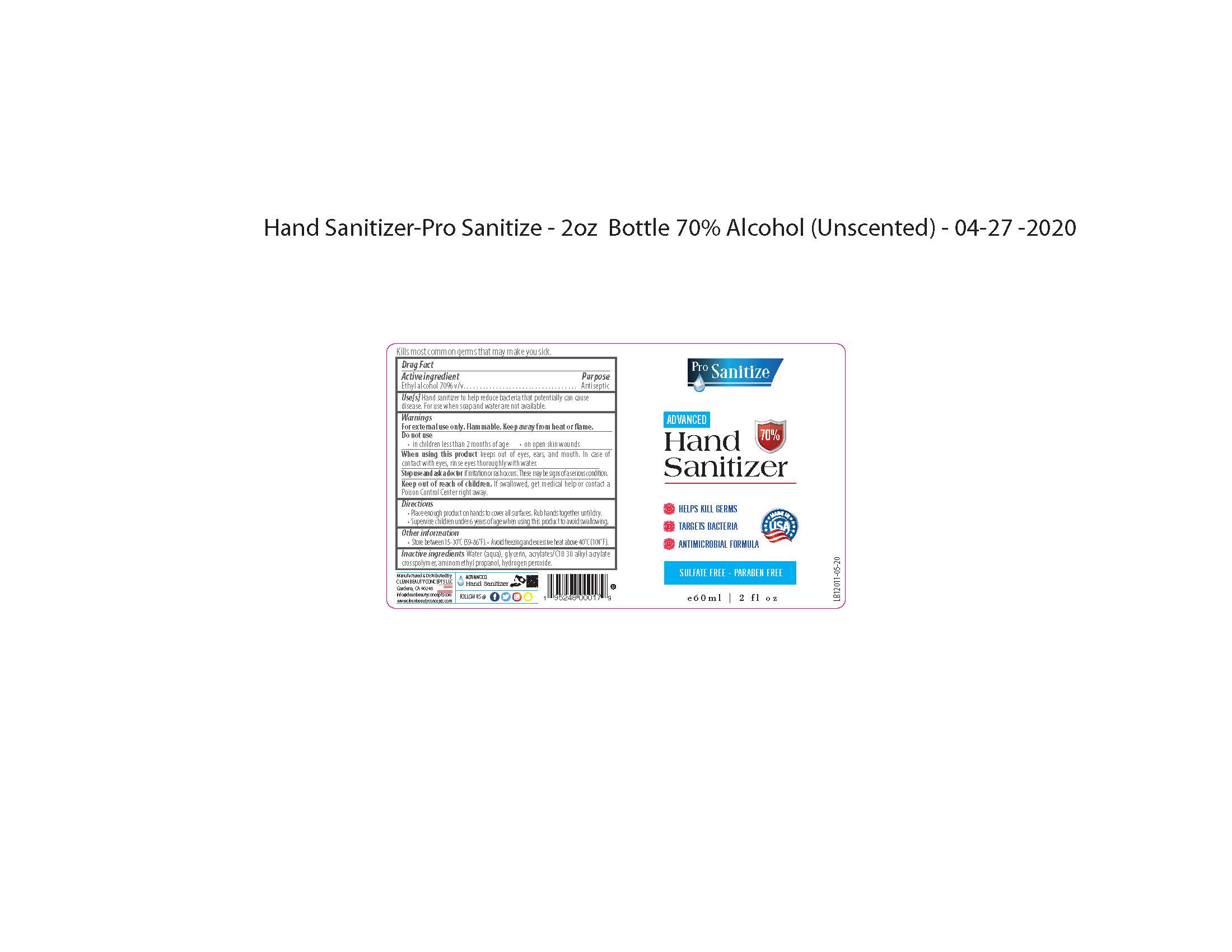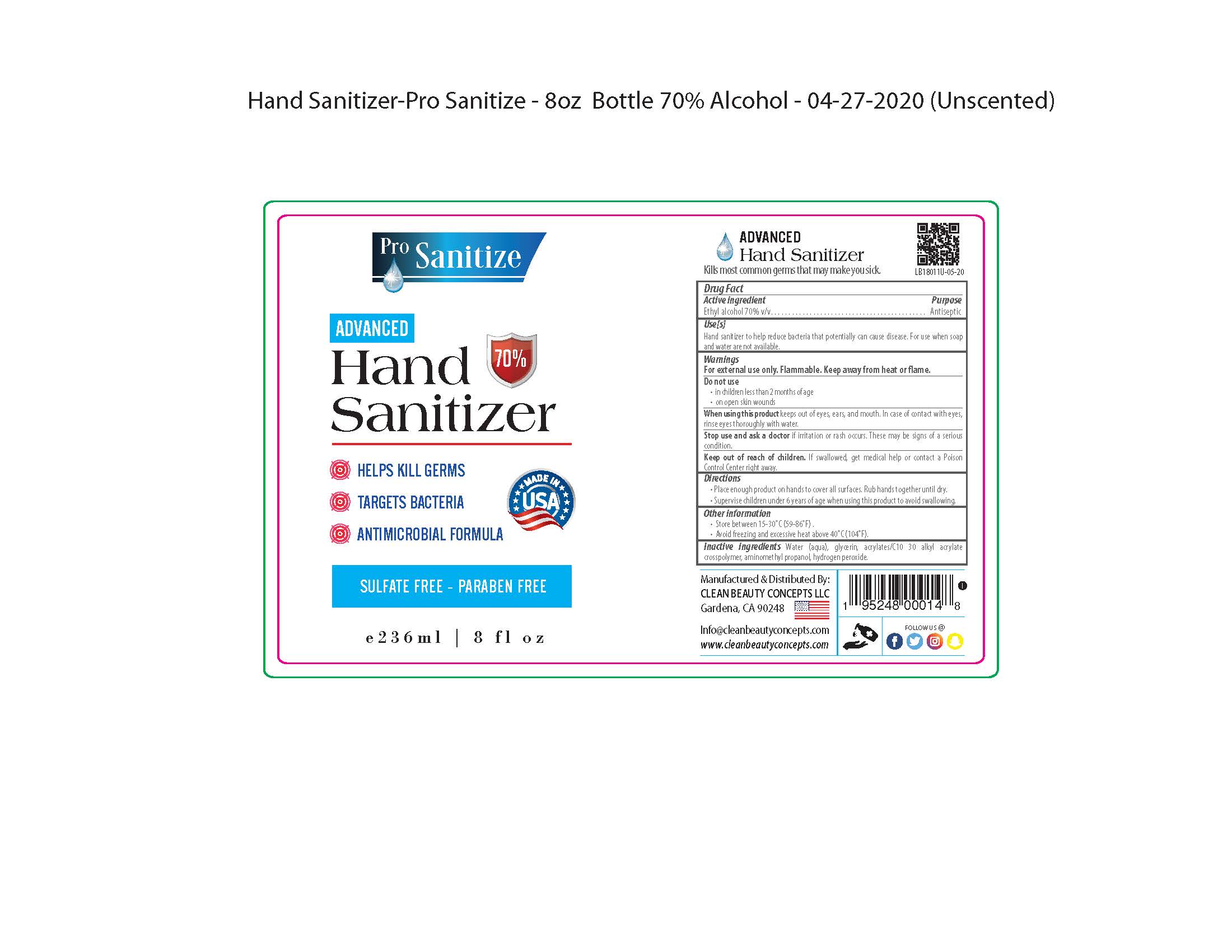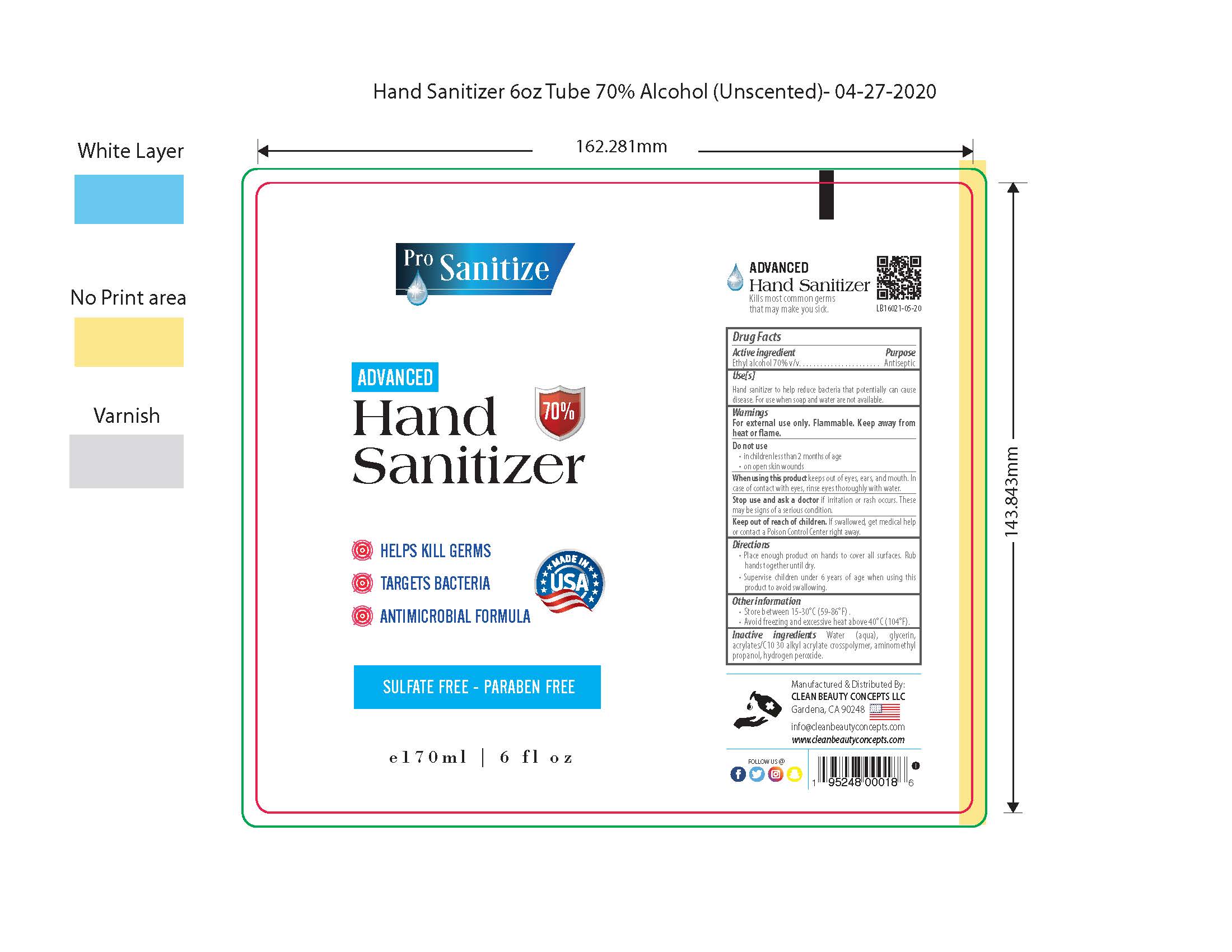 DRUG LABEL: Pro-Sanitize
NDC: 76665-001 | Form: LIQUID
Manufacturer: Clean Beauty Concepts
Category: otc | Type: HUMAN OTC DRUG LABEL
Date: 20200423

ACTIVE INGREDIENTS: ALCOHOL 70 mL/100 mL
INACTIVE INGREDIENTS: AMINOMETHYLPROPANOL 0.085 mL/100 mL; WATER 28.14 mL/100 mL; GLYCERIN 1.45 mL/100 mL; HYDROGEN PEROXIDE 0.125 mL/100 mL; CARBOMER INTERPOLYMER TYPE A (ALLYL SUCROSE CROSSLINKED) 0.2 mL/100 mL

unclassified section

The hand sanitizer is manufactured using only the following United States Pharmacopoeia (USP) grade ingredients:

a. Alcohol (ethanol) (USP or Food Chemical Codex (FCC) grade) (70%, volume/volume (v/v)) in an aqueous solution denatured according to Alcohol and Tobacco Tax and Trade Bureau regulations in 27 CFR part 20.

b. Glycerol (1.45% v/v).

c. Hydrogen peroxide (0.125% v/v).

d. Sterile distilled water or boiled cold water.

e. Acrylates/C10 30 Alkyl acrylate crosspolymer(.20% v/v)

f. Aminomethyl propanol (.085% v/v)

active ingredient

Alcohol 70% v/v. Purpose: Antiseptic

use

Hand Sanitizer to help reduce bacteria that potentially can cause disease. For use when soap and water are not available.

warning

For external use only. Flammable. Keep away from heat or flame

do not use

· in children less than 2 months of age

· on open skin wounds

when using section

When using this product keep out of eyes, ears, and mouth. In case of contact with eyes, rinse eyes thoroughly with water.
Stop use and ask a doctor if irritation or rash occurs. These may be signs of a serious condition.
Keep out of reach of children. If swallowed, get medical help or contact a Poison Control Center right away.

stop use section

Stop use and ask a doctor if irritation or rash occurs. These may be signs of a serious condition.

Keep out of reach of children. If swallowed, get medical help or contact a Poison Control Center right away.

directions

· Place enough product on hands to cover all surfaces. Rub hands together until dry.

· Supervise children under 6 years of age when using this product to avoid swallowing.

other information

· Store between 15-30C (59-86F)

· Avoid freezing and excessive heat above 40C (104F)

inactive ingredients

water(aqua), glycerin, acrylates/C10 30 alkyl acrylate crosspolymer, aminomethyl propanol, hydrogen peroxide

Purpose

Antiseptic

packaging

60 ML NDC: 76665-001-02

170 ML NDC: 76665-001-06

236 ML NDC: 76665-001-08

3785 ML NDC: 76665-001-01